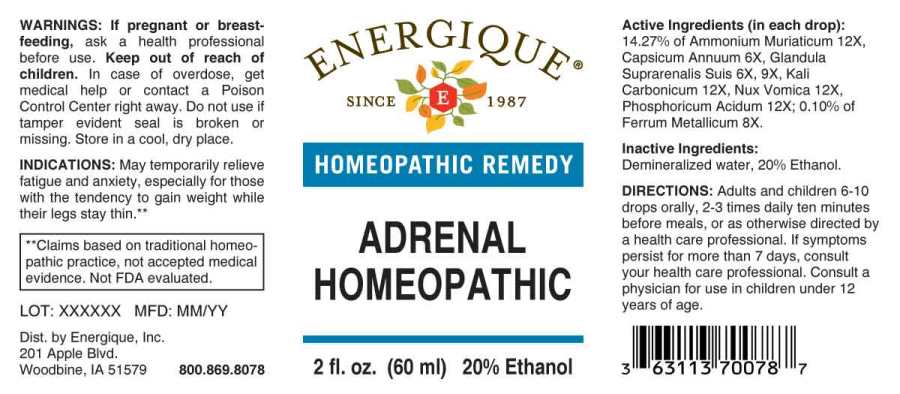 DRUG LABEL: Adrenal Homeopathic
NDC: 44911-0188 | Form: LIQUID
Manufacturer: Energique, Inc.
Category: homeopathic | Type: HUMAN OTC DRUG LABEL
Date: 20240716

ACTIVE INGREDIENTS: CAPSICUM 6 [hp_X]/1 mL; SUS SCROFA ADRENAL GLAND 6 [hp_X]/1 mL; IRON 8 [hp_X]/1 mL; AMMONIUM CHLORIDE 12 [hp_X]/1 mL; POTASSIUM CARBONATE 12 [hp_X]/1 mL; STRYCHNOS NUX-VOMICA SEED 12 [hp_X]/1 mL; PHOSPHORIC ACID 12 [hp_X]/1 mL
INACTIVE INGREDIENTS: WATER; ALCOHOL

DRUG FACTS:

ACTIVE INGREDIENTS:

(in each drop): 14.27% of Ammonium Muriaticum 12X, Capsicum Annuum 6X, Glandula Suprarenalis Suis 6X, 9X, Kali Carbonicum 12X, Nux Vomica 12X, Phosphoricum Acidum 12X; 0.10% of Ferrum Metallicum 8X.

INDICATIONS:

May temporarily relieve fatigue and anxiety, especially for those with the tendency to gain weight while their legs stay thin.**

**Claims based on traditional homeopathic practice, not accepted medical evidence. Not FDA evaluated.

WARNINGS:

If pregnant or breast-feeding, ask a health professional before use.

Keep out of reach of children. In case of overdose, get medical help or contact a Poison Control Center right away.

Do not use if tamper evident seal is broken or missing. Store in a cool, dry place.

KEEP OUT OF REACH OF CHILDREN:

In case of overdose, get medical help or contact a Poison Control Center right away.

DIRECTIONS:

Adults and children 6-10 drops orally, 2-3 times daily ten minutes before meals, or as otherwise directed by a health care professional. If symptoms persist for more than 7 days, consult your health care professional. Consult a physician for use in children under 12 years of age.

INDICATIONS:

May temporarily relieve fatigue and anxiety, especially for those with the tendency to gain weight while their legs stay thin.**

**Claims based on traditional homeopathic practice, not accepted medical evidence. Not FDA evaluated.

INACTIVE INGREDIENTS:

Demineralized water, 20% Ethanol.

QUESTIONS:

Dist. by Energique, Inc.

201 Apple Blvd.

Woodbine, IA 51579 800.869.8078

PACKAGE LABEL DISPLAY:

ENERGIQUE

SINCE 1987

HOMEOPATHIC REMEDY

ADRENAL

HOMEOPATHIC

2 fl. oz. (60 ml)